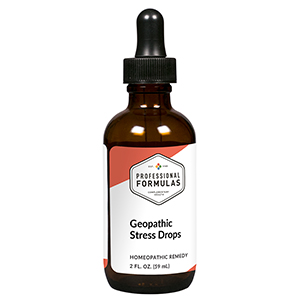 DRUG LABEL: Geopathic Stress Drops
NDC: 63083-2096 | Form: LIQUID
Manufacturer: Professional Complementary Health Formulas
Category: homeopathic | Type: HUMAN OTC DRUG LABEL
Date: 20190815

ACTIVE INGREDIENTS: IODINE 4 [hp_X]/59 mL; AGAVE AMERICANA LEAF 6 [hp_X]/59 mL; COPPER 6 [hp_X]/59 mL; PHOSPHORUS 18 [hp_X]/59 mL; CORALLIUM RUBRUM EXOSKELETON 1000 [hp_X]/59 mL; FERROSOFERRIC OXIDE 30 [hp_X]/59 mL
INACTIVE INGREDIENTS: ALCOHOL; WATER

C96

ACTIVE INGREDIENTS

Iodium 4X
Agave americana 6X
Cuprum metallicum 6X, 12X, 30X
Phosphorus 18X
Corallium rubrum 1000X
and all the following imponderables at 30X, 100X:
Cosmic ray
Earth magnetic
Pathogenic radiation

QUESTIONS

Professional Formulas

PO Box 2034 Lake Oswego, OR 97035

INDICATIONS

For temporary relief of occasional headaches, minor muscle or joint pain, fatigue or lethargy, difficulty with concentration, insomnia, or sensitivity to changes in weather.*

PURPOSE

*Claims based on traditional homeopathic practice, not accepted medical evidence. Not FDA evaluated.

WARNINGS

In case of overdose, get medical help or contact a poison control center right away.

Keep out of the reach of children.

PREGNANCY OR BREAST FEEDING

If pregnant or breastfeeding, ask a healthcare professional before use.

DIRECTIONS

Place drops under tongue 30 minutes before/after meals. Adults and children 12 years and over: Take 10 drops up to 3 times per day. Consult a physician for use in children under 12 years of age.

OTHER INFORMATION

Tamper resistant. If seal is broken, do not use. After opening, close container tightly and store at room temperature away from heat.

INACTIVE INGREDIENTS

20% ethanol, purified water.

LABEL

Est 1985

Professional Formulas

Complementary Health

Geopathic Stress Drops

Homeopathic Remedy

2 FL. OZ. (59 mL)